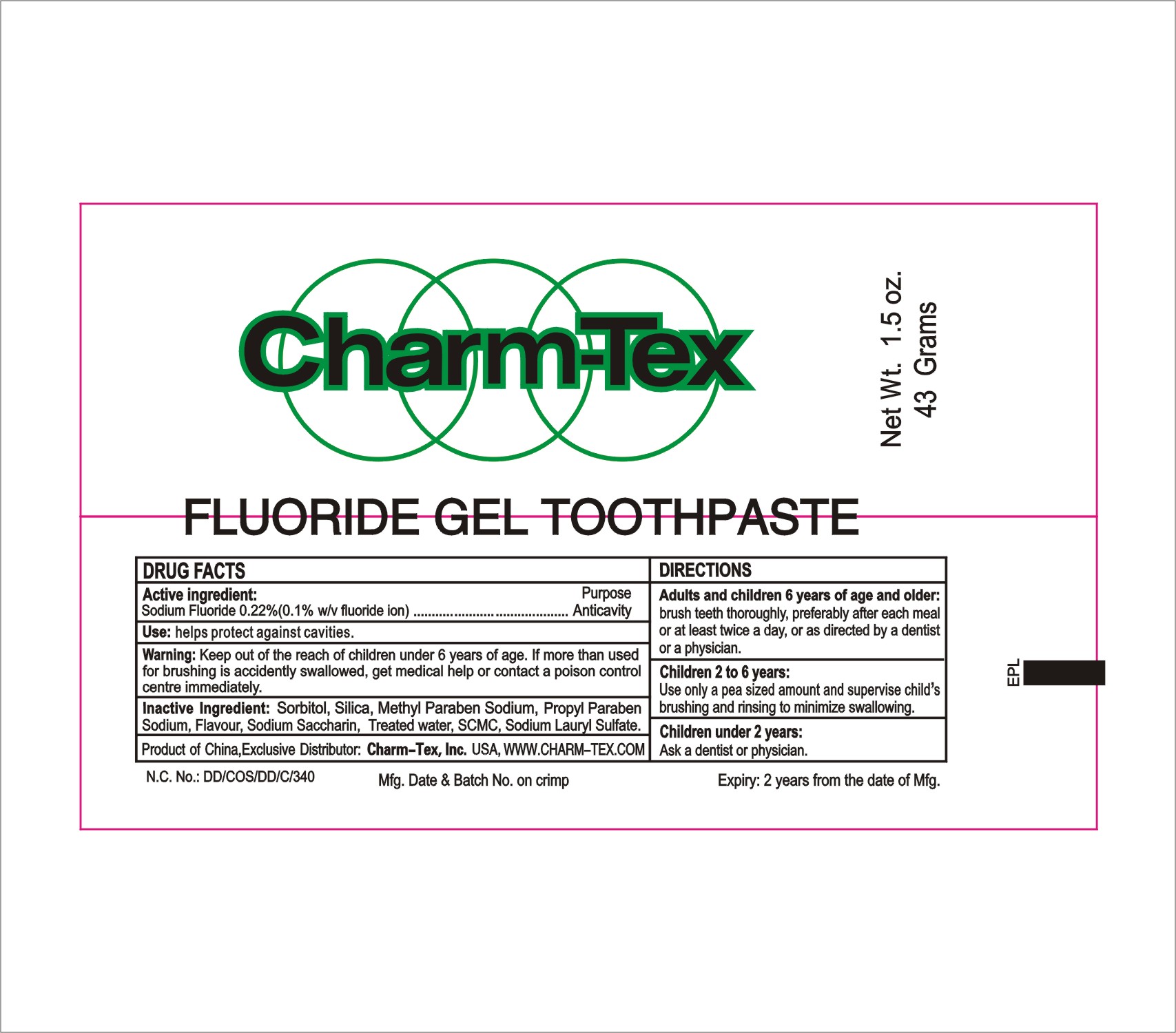 DRUG LABEL: Fluoride Gel
NDC: 73343-002 | Form: PASTE
Manufacturer: Yangzhou Tracey Daily Chemical Plastic Co., Ltd.
Category: otc | Type: HUMAN OTC DRUG LABEL
Date: 20191014

ACTIVE INGREDIENTS: SODIUM FLUORIDE 0.22 g/100 g
INACTIVE INGREDIENTS: CARBOCYSTEINE LYSINE MONOHYDRATE; SORBITOL; SODIUM LAURYL SULFATE; METHYL PARAOXON; PROPYLPARABEN SODIUM; WATER; SODIUM SILICATE; POTASSIUM SODIUM SACCHARATE

Charm-Tex Fluoride Gel Toothpaste 73343-002

Active ingredients

Sodium Fluoride 0.22%(0.1 w/v Fluoride ion)

Purpose

anticavity

Uses

helps protect against cavities.

Warnings

Keep out of the reach of children under 6 years of age.if more than used for brushing is accidently swallowed,get medical help or contact a Poison Control Center immediately.

Keep out of reach of children.

Directions

Adults and children 2years of age and older:Brush teeth thoroughly,preferably after each meal or at least twice a day,or as directed by a dentist or a physician.

Children 2-6 years:Use only a pea sized amount and supervise child's brushing and rinsing (to minimize swallowing)

Children under 2 years:Ask a dentist or a physician.

INACTIVE INGREDIENT

Sorbitol,Silica,methyl Paraben Sodium,Propyl Paraben Sodium ,Flavour ,Sodium Saccharin,Treated Water,SCMC,Sodium Lauryl Sulfate